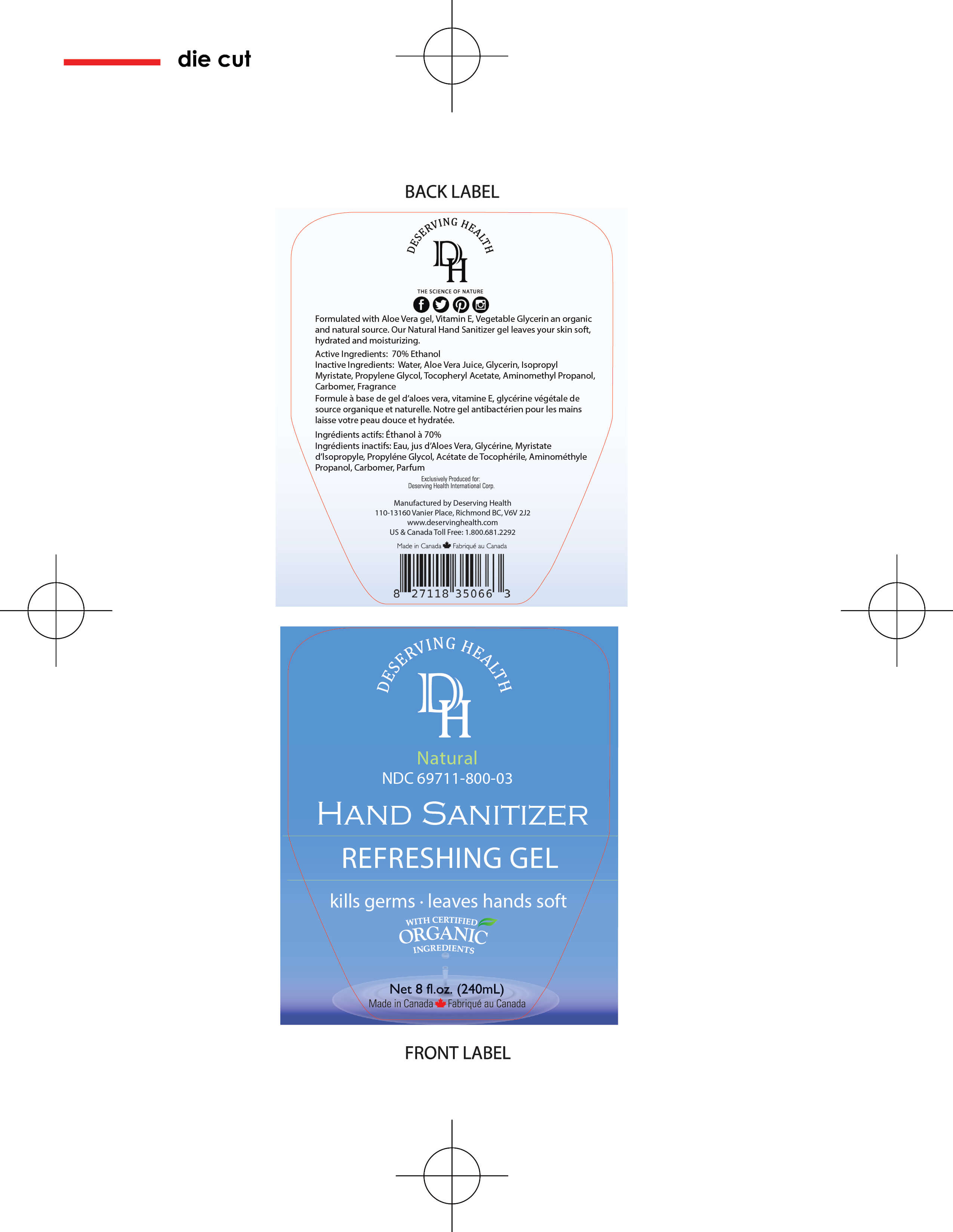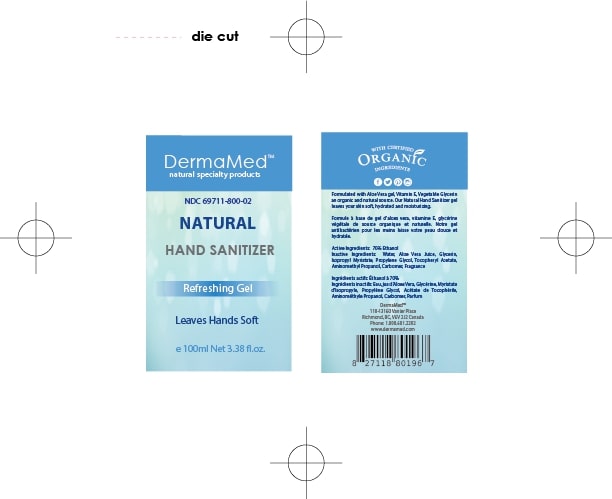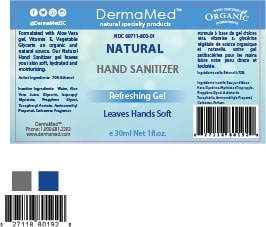 DRUG LABEL: DermaMed Natural Hand Sanitizer
NDC: 69711-800 | Form: GEL
Manufacturer: Biological Health Group
Category: otc | Type: HUMAN OTC DRUG LABEL
Date: 20200424

ACTIVE INGREDIENTS: ALCOHOL 70 mL/100 mL
INACTIVE INGREDIENTS: CARBOMER COPOLYMER TYPE A; WATER; 1,2-PROPANEDITHIOL; ALOE VERA LEAF; AMINOMETHYLPROPANOL; .ALPHA.-TOCOPHEROL ACETATE, D-; ISOPROPYL MYRISTATE; GLYCERIN

DM Hand Sanitizer

ACTIVE INGREDIENT

Ethyl Alcohol 70% v/v

PURPOSE

Antimicrobial

WHEN USING

Hand sanitizer to help reduce bacteria on the skin that could cause disease
Recommended for repeated use

WARNINGS

Flammable. Keep away from fire or flame.

For external use only

When using this product do not use in or near the eyes. In case of contact, rinse eyes thoroughly with water.

Stop use and ask a doctor if irritation or rash appears and lasts

Keep out of reach of children. If swallowed, get medical help or contact a Poison Control Center right away.

INDICATIONS AND USAGE

Place enough product in your palm to thoroughly cover your hands
Rub hands together briskly until dry
No rinsing required
No towels needed

INACTIVE INGREDIENT

Water, Aloe Vera Juice, Glycerin, Isopropyl Myristate,Tocopheryl Acetate, Acrylates/C10-30 Alkyl Acrylate Crosspolymer,Aminomethyl Propanol, Propylene Glycol, Fragrance